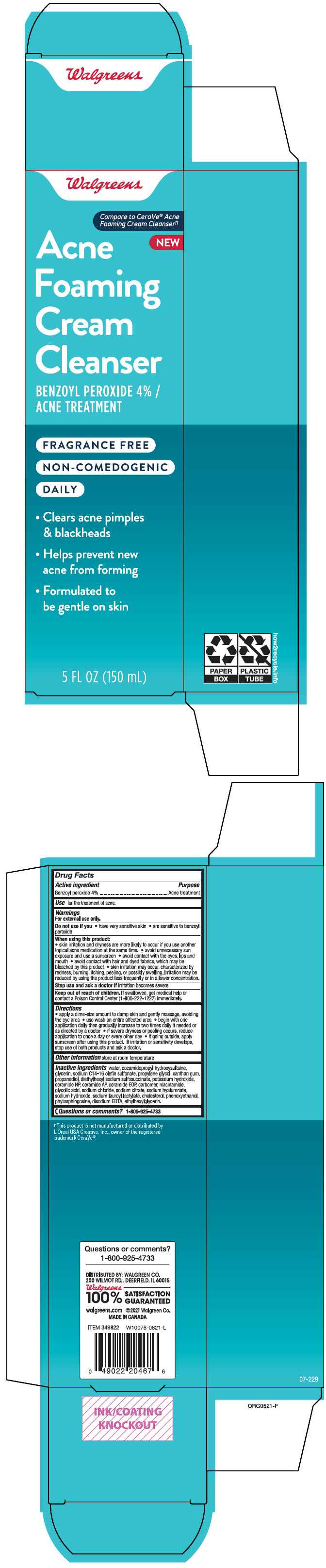 DRUG LABEL: Walgreens Acne Foaming Cleanser
NDC: 0363-0467 | Form: CREAM
Manufacturer: Walgreen Company
Category: otc | Type: HUMAN OTC DRUG LABEL
Date: 20241030

ACTIVE INGREDIENTS: Benzoyl Peroxide 40 mg/1 mL
INACTIVE INGREDIENTS: Water; Cocamidopropyl Hydroxysultaine; Glycerin; Sodium C14-16 Olefin Sulfonate; Propylene Glycol; Xanthan Gum; Propanediol; DOCUSATE SODIUM; Potassium Hydroxide; Ceramide NP; Ceramide AP; CERAMIDE 1; CARBOMER HOMOPOLYMER, UNSPECIFIED TYPE; Niacinamide; Glycolic Acid; Sodium Chloride; SODIUM CITRATE, UNSPECIFIED FORM; HYALURONATE SODIUM; Sodium Hydroxide; Sodium Lauroyl Lactylate; Cholesterol; Phenoxyethanol; PHYTOSPHINGOSINE; EDETATE DISODIUM; Ethylhexylglycerin

Walgreens Acne Foaming Cream Cleanser
Acne Treatment

Drug Facts

Active ingredient

Benzoyl Peroxide 4%

Purpose

Acne Treatment

Use

for the treatment of acne.

Warnings

For external use only.

Do not use if you

- have very sensitive
- are sensitive to benzoyl peroxide

When using this product

- skin irritation and dryness are more likely to occur if you use another topical acne medication at the same time
- avoid unnecessary sun exposure and use a sunscreen
- avoid contact with the eyes, lips and mouth
- avoid contact with hair and dyed fabrics, which may be bleached by this product
- skin irritation may occur, characterized by redness, burning, itching, peeling, or possibly swelling. Irritation may be reduced by using the product less frequently or in a lower concentration.

Stop use and ask a doctor if irritation becomes severe

Keep out of reach of children. If swallowed, get medical help or contact a Poison Control Center (1-800-222-1222) immediately.

Directions

- apply a dime-size amount to damp skin and gently massage, avoiding the eye area
- use wash on entire affected area
- begin with one application daily then gradually increase to two times daily if needed or as directed by a doctor
- if severe dryness or peeling occurs, reduce application to once a day or every other day
- if going outside, apply sunscreen after using this product. If irritation or sensitivity develops, stop use of both products and ask a doctor.

Other information

Store at room temperature

Inactive ingredients

water, cocamidopropyl hydroxysultaine, glycerin, sodium C14-16 olefin sulfonate, propylene glycol, xanthan gum, propanediol, diethylhexyl sodium sulfosuccinate, potassium hydroxide, ceramide NP, ceramide AP, ceramide EOP, carbomer, niacinamide, glycolic acid, sodium chloride, sodium citrate, sodium hyaluronate, sodium lauroyl lactylate, cholesterol, phenoxyethanol, phytosphingosine, disodium EDTA, ethylhexylglycerin.

Questions or comments?

1-800-925-4733

DISTRIBUTED BY: WALGREEN CO.
200 WILMOT RD., DEERFIELD, IL 60015

PRINCIPAL DISPLAY PANEL - 150 mL Tube Carton

Walgreens

Compare to CeraVe® Acne
Foaming Cream Cleanser††

NEW
Acne
Foaming
Cream
Cleanser

BENZOYL PEROXIDE 4% /
ACNE TREATMENT

FRAGRANCE FREE

NON-COMEDOGENIC

DAILY

- Clears acne pimples
  & blackheads
- Helps prevent new
  acne from forming
- Formulated to
  be gentle on skin

5 FL OZ (150 mL)